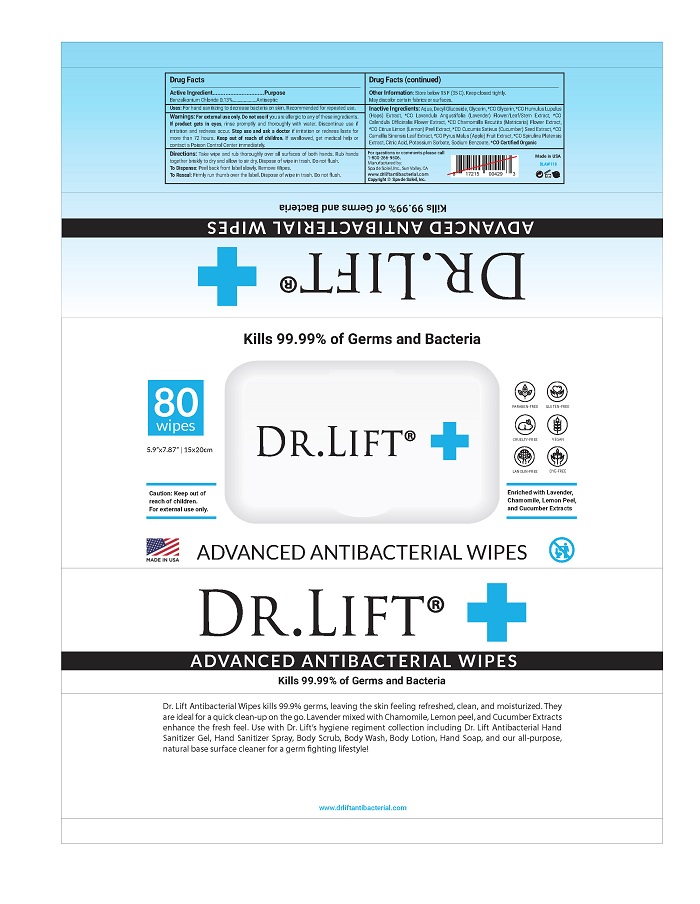 DRUG LABEL: Dr Lift Advanced Antibacterial Wipes
NDC: 68062-2244 | Form: LIQUID
Manufacturer: Spa de Soleil
Category: otc | Type: HUMAN OTC DRUG LABEL
Date: 20200917

ACTIVE INGREDIENTS: BENZALKONIUM CHLORIDE 0.156 mg/120 mg
INACTIVE INGREDIENTS: GLYCERIN; WATER

Dr Lift Advanced Antibacterial Wipes

Active Ingredient

Benzalkonium Chloride 0.13%

Purpose

Antiseptic

Warnings

For external use only. Do not use if you are allergic to any of these ingredients. If product gets in eyes, rinse promptly and thoroughly with water. Discontinue use if irritation and redness occur. Stop use and ask a doctor if irritation or redness lasts for more than 72 hours. Keep out of reach of children. If swallowed, get medical help or contact a Poison Control Center immediately.

Keep out of reach of children.

Directions

Take wipe and rub thoroughly over all surfaces of both hands. Rub hands together briskly to dry and allow to air dry. Dispose of wipe in trash. Do not flush.

To Dispense: Peel back front label slowly. Remove Wipes.

To Reseal: Firmly run thumb over the label. Dispose of wipe in trash. Do not flush.

DOSAGE AND ADMINISTRATION

Place enough product in the palm of your hands to thoroughly cover you hands. Rub hands together briskly until product is completely absorbed and hands are dry.

Inactive Ingredients:

Inactive Ingredients

Aqua, Decyl Glucoside, Glycerin, *CO Glycerin, *CO Humulus Lupulus (Hops) Extract, *CO Lavandula Angustifolia (Lavender) Flower/Leaf/Stem Extract, *CO Calendula Officinalis Flower Extract, *CO Chamomilla Recutita (Matricaria) Flower Extract, *CO Citrus Limon (Lemon) Peel Extract, *CO Cucumis Sativus (Cucumber) Seed Extract, *CO Camellia Sinensis Leaf Extract, *CO Pyrus Malus (Apple) Fruit Extract, *CO Spirulina Platensis Extract, Citric Acid, Potassium Sorbate, Sodium Benzoate. *CO Certified Organic